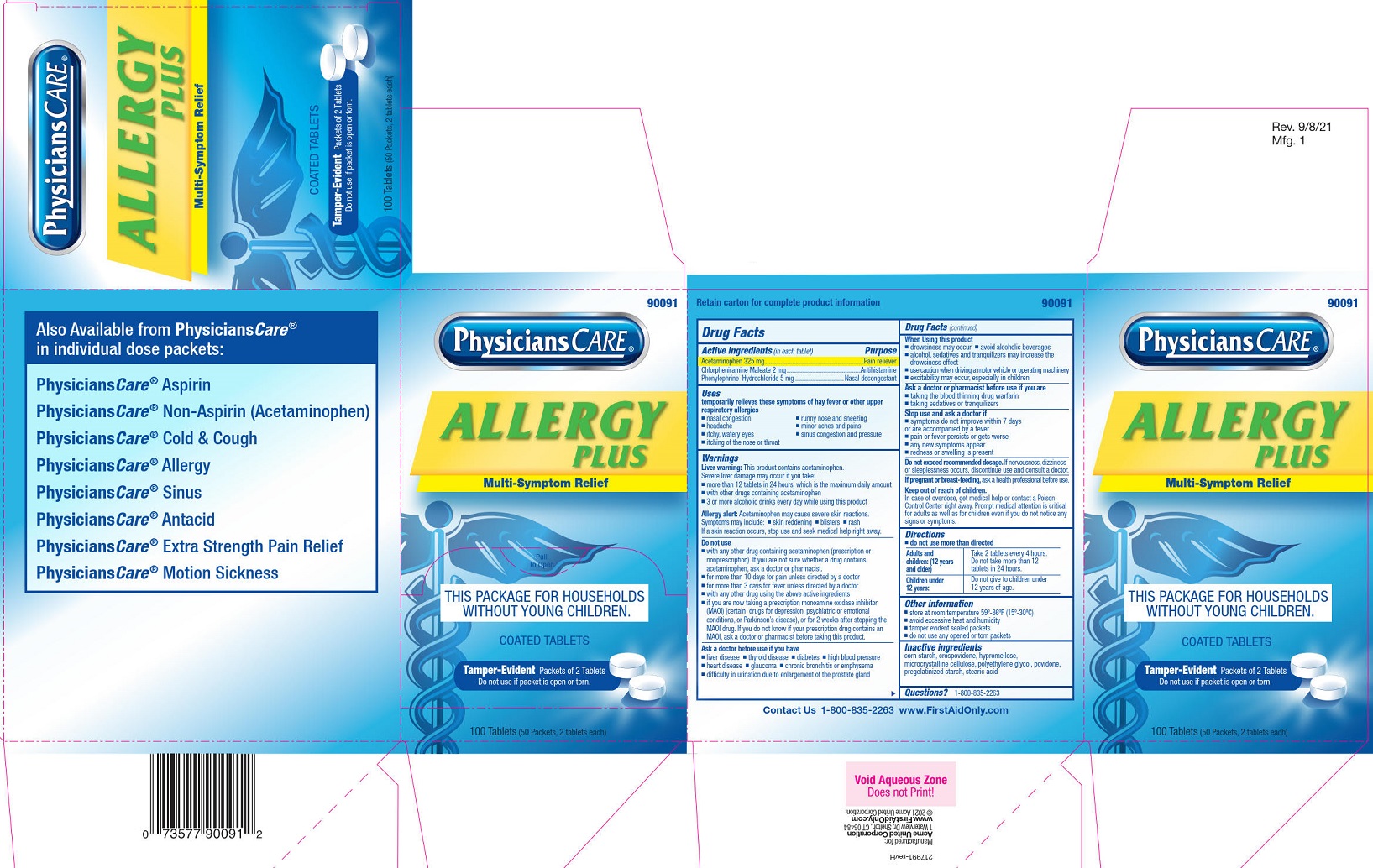 DRUG LABEL: PhysiciansCare Allergy
NDC: 0924-0091 | Form: TABLET, FILM COATED
Manufacturer: Acme United Corporation
Category: otc | Type: HUMAN OTC DRUG LABEL
Date: 20250908

ACTIVE INGREDIENTS: ACETAMINOPHEN 325 mg/1 1; CHLORPHENIRAMINE MALEATE 2 mg/1 1; PHENYLEPHRINE HYDROCHLORIDE 5 mg/1 1
INACTIVE INGREDIENTS: POVIDONE; CELLULOSE, MICROCRYSTALLINE; HYPROMELLOSES; POLYETHYLENE GLYCOL, UNSPECIFIED; STARCH, CORN; STEARIC ACID; CROSPOVIDONE

Physicians Care Allergy

Drug Facts

Active ingredients (in each tablet)

Acetaminophen 325 mg
Chlorpheniramine Maleate 2 mg
Phenylephrine Hydrochloride 5 mg

Purpose

Pain reliever/fever reduecer
Antihistamine
Nasal decongestant

Uses

temporarily relieves these symptoms of hay fever or other upper respiratory allergies

- nasal congestion
- headache
- itchy, watery eyes
- itching of the nose and throat
- running nose and sneezing
- minor aches and pains
- sinus congestion and pressure

Warnings

Liver warning: This product contains acetaminophen. Severe liver damage may occur if you take:

■ more than 4,000 mg of acetaminophen in 24 hours, which is the maximum daily amount

■ with other drugs containing acetaminophen

■ 3 or more alcoholic drinks every day while using this product

Allergy alert: Acetaminophen may cause severe skin reactions. Symptoms may include:

■ skin reddening

■ blisters

■ rash

If a skin reaction occurs, stop use and seek medical help right away.

Do not use

■ with any other drug containing acetaminophen (prescription or nonprescription). If you are not sure whether a
drug contains acetaminophen, ask a doctor or pharmacist.

■ for more than 10 days for pain unless directed by a doctor

■ for more than 3 days for fever unless directed by a doctor

■ with any other drug using the above active ingredients

■ if you are now taking a prescription monoamine oxidase inhibitor (MAOI) (certain drugs for depression,
psychiatric or emotional conditions, or Parkinson’s disease), or for 2 weeks after stopping the MAOI drug. If you
do not know if your prescription drug contains an MAOI, ask a doctor or pharmacist before taking this product.

Ask a doctor before use if you have

■ liver disease

■ thyroid disease

■ diabetes

■ high blood pressure

■ heart disease

■ glaucoma

■ chronic bronchitis or emphysema

■ difficulty in urination due to enlargement of the prostate gland

When using this product

■ drowsiness may occur

■ avoid alcoholic beverages

■ alcohol, sedatives and tranquilizers may increase the drowsiness effect

■ use caution when driving a motor vehicle or operating machinery

■ excitability may occur, especially in children

Ask a doctor or pharmacist before use if you are

■ taking the blood thinning drug warfarin

■ taking sedatives or tranquilizers

Stop use and ask a doctor if

■ symptoms do not improve within 7 days or are accompanied by a fever

■ pain or fever persists or gets worse

■ any new symptoms appear

■ redness or swelling is present

PREGNANCY OR BREAST FEEDING

If pregnant or breast-feeding, ask a health professional before use.

Keep out of the reach of children.

In case of overdose, get medical help or contact a Poison Control Center right away. Prompt medical attention is critical for adults as well as for children even if you do not notice any signs or symptoms.

Directions

- do not use more than directed

Adults and children: (12 years and older)

Take 2 tablets every 4 hours. Do not take more than 12 tablets in 24 hours.

Children under 12 years:

Do not give to children under 12 years of age.

Other information

- store at room temperature 59º-86ºF (15º-30ºC)
- avoid excessive heat and humidity
- tamper-evident sealed packets
- do not use any opened or torn packets

Inactive ingredients

corn starch, crospovidone, hypromellose, microcrystalline cellulose, polyethylene glycol, povidone, pregelatinized starch, stearic acid

Questions?

1-800-835-2263

Allergy Plus Label

90091

Physicians Care®

Allergy Plus

Multi-Symptom Relief

Pull To Open

This Package For Households Without Young Children.

COATED TABLETS

Tamper-Evident Packets of 2 Tablets

Do not use if packet is open or torn.

100 Tablets (50 Packets, 2 tablets each)